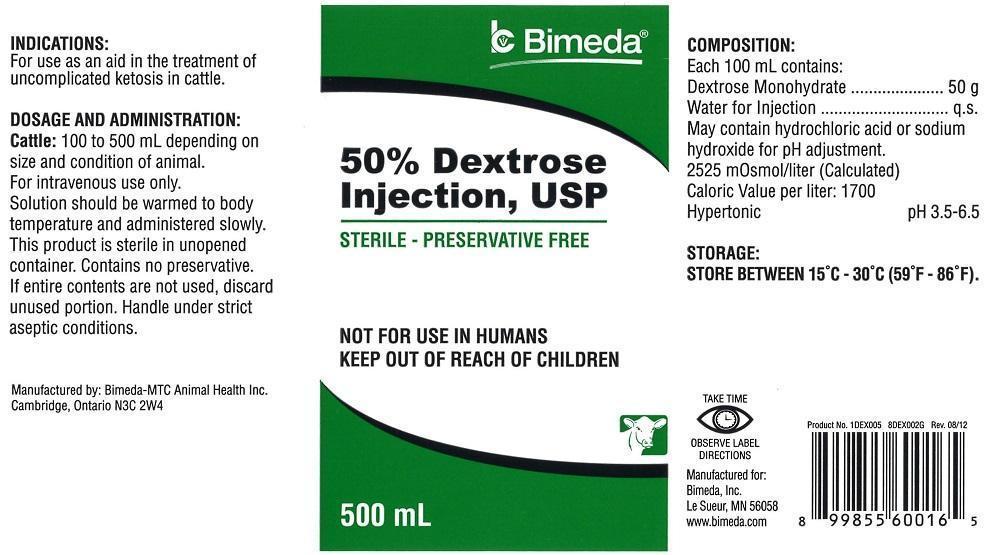 DRUG LABEL: Dextrose
NDC: 61133-0295 | Form: INJECTION
Manufacturer: Bimeda, Inc.
Category: animal | Type: OTC ANIMAL DRUG LABEL
Date: 20211222

ACTIVE INGREDIENTS: DEXTROSE MONOHYDRATE 50 g/100 mL

INDICATIONS:

For use as an aid in the treatment of uncomplicated ketosis in cattle.

DOSAGE AND ADMINISTRATION:

Cattle: 100 to 500 mL depending on size and condition of animal. For intravenous use only. Solution should be warmed to body temperature and administered slowly. This product is sterile in unopened container. Contains no preservative. If entire contents are not used, discard unused portion. Handle under strict aseptic conditions.

DESCRIPTION

COMPOSITION:

Each 100 mL contains:

Dextrose Monohydrate ...............50 g

Water for Injection.....................q.s.

May contain hydrochloric acid or sodium hydroxide for pH adjustment.

2525 m0smol/liter (Calculated)

Caloric Value per liter: 1700

Hypertonic pH 3.5-6.5

STORAGE:

STORE BETWEEN 15°C-30°C (59°F-86°F).